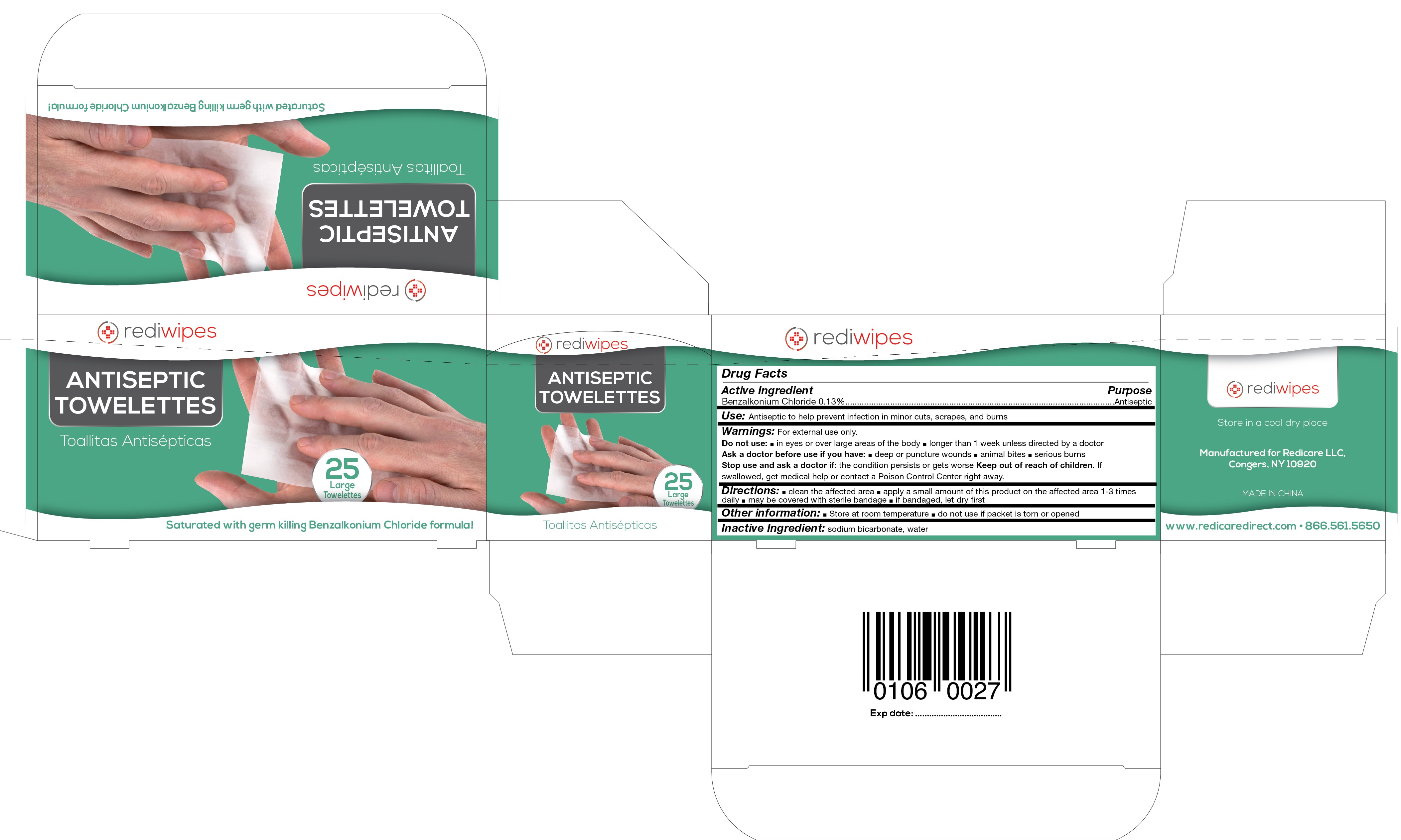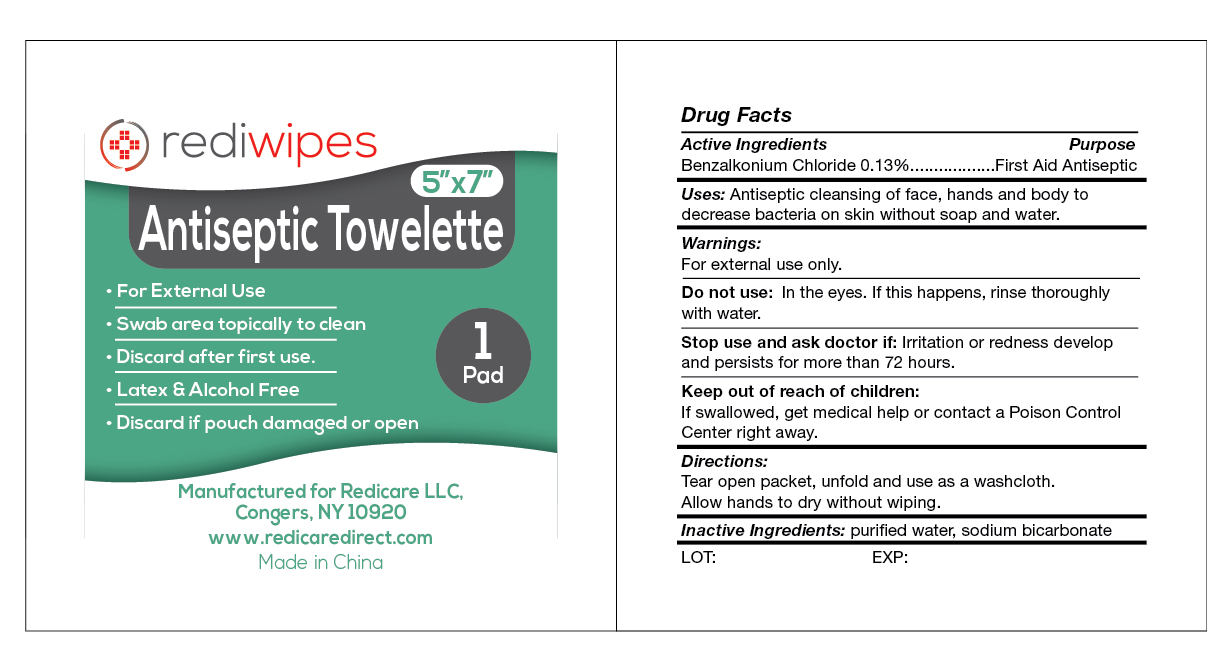 DRUG LABEL: Rediwipes Antiseptic Cleaning Towelettes
NDC: 71105-323 | Form: SWAB
Manufacturer: Redicare LLC
Category: otc | Type: HUMAN OTC DRUG LABEL
Date: 20221012

ACTIVE INGREDIENTS: BENZALKONIUM CHLORIDE 0.13 g/100 g
INACTIVE INGREDIENTS: SODIUM BICARBONATE; WATER

BZK Wipes

Active Ingredients...................................Uses

Benzalkonium Chloride 0.13%................................First Aid Antiseptic

Uses:

Antiseptic cleansing of face, hands and body to decrease bacteria on skin without soap and water. Antiseptic to help prevent further infection in minor cuts, scrapes, and burns.

Warnings

For external use only.

Do not use:

- In the eyes. If this happens, rinse thoroughly with water.
- Over large areas of the body
- Longer than 1 week unless directed by a doctor

Stop use and ask doctor if:

- Irritation of redness develop and persists for more than 72 hours.
- the condition persists or gets worse

Keep out of reach of children:

If swallowed, get medical help or contact a Poison Control Center right away.

Ask a doctor before use if you have:

- Deep or puncture wounds
- Animal bites
- Serious burns

Directions:

Tear open packet, unfold and use as a washcloth. Allow hands to dry without wiping.

Inactive Ingredients:

purified water, sodium bicarbonate

Other information:

- For external use only.
- Store at room temperature
- Do not use if packet is torn or opened